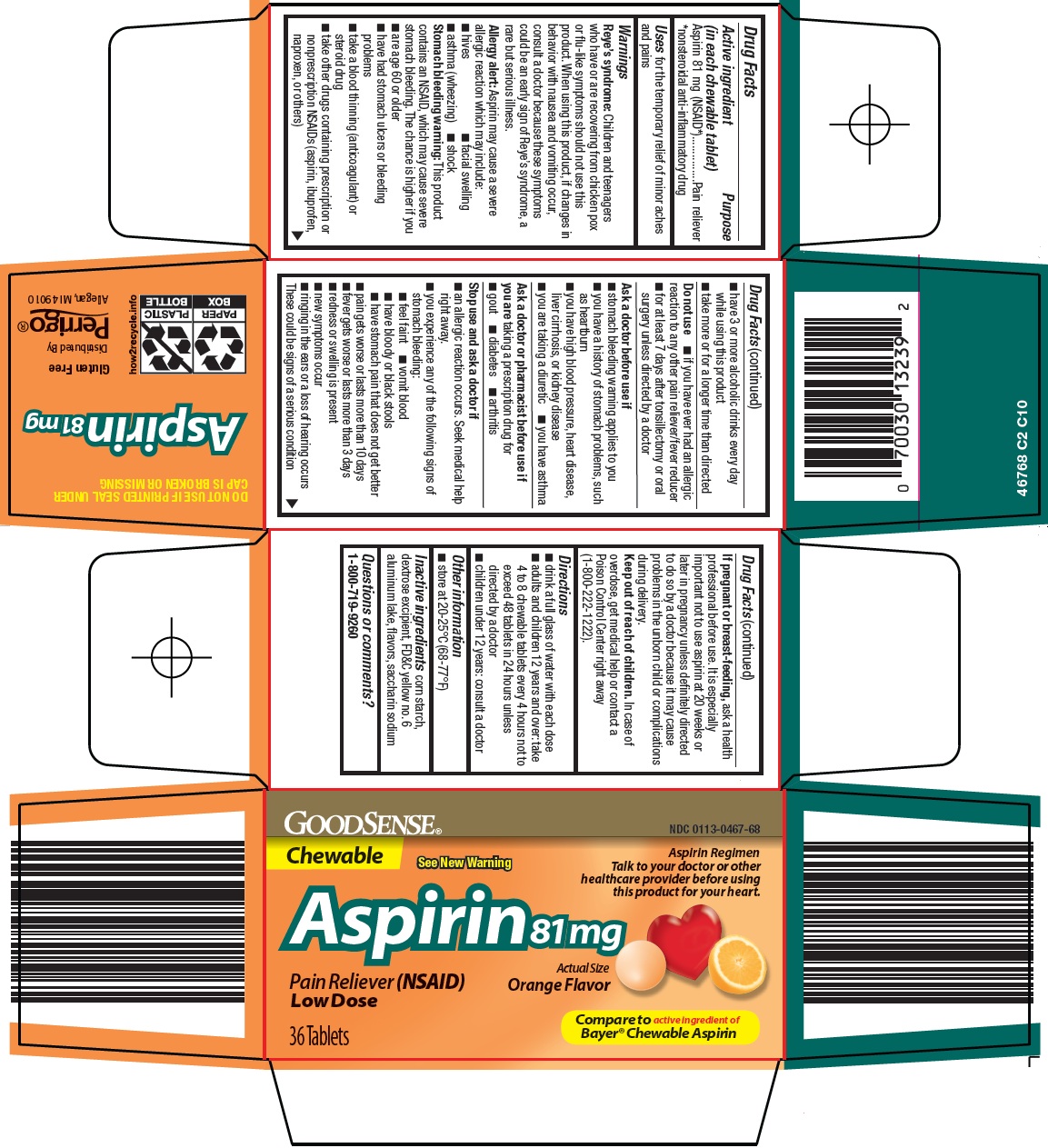 DRUG LABEL: good sense aspirin
NDC: 0113-0467 | Form: TABLET, CHEWABLE
Manufacturer: L. Perrigo Company
Category: otc | Type: HUMAN OTC DRUG LABEL
Date: 20260207

ACTIVE INGREDIENTS: ASPIRIN 81 mg/1 1
INACTIVE INGREDIENTS: STARCH, CORN; FD&C YELLOW NO. 6 ALUMINUM LAKE; SACCHARIN SODIUM

Perrigo Aspirin Drug Facts

Active ingredient (in each chewable tablet)

Aspirin 81 mg (NSAID*)

*nonsteroidal anti-inflammatory drug

Purpose

Pain reliever

Uses

for the temporary relief of minor aches and pains

Warnings

Reye’s syndrome: Children and teenagers who have or are recovering from chicken pox or flu-like symptoms should not use this product. When using this product, if changes in behavior with nausea and vomiting occur, consult a doctor because these symptoms could be an early sign of Reye’s syndrome, a rare but serious illness.

Allergy alert: Aspirin may cause a severe allergic reaction which may include:

- hives
- facial swelling
- asthma (wheezing)
- shock

Stomach bleeding warning: This product contains an NSAID, which may cause severe stomach bleeding. The chance is higher if you

- are age 60 or older
- have had stomach ulcers or bleeding problems
- take a blood thinning (anticoagulant) or steroid drug
- take other drugs containing prescription or nonprescription NSAIDs (aspirin, ibuprofen, naproxen, or others)
- have 3 or more alcoholic drinks every day while using this product
- take more or for a longer time than directed

Do not use

1. if you have ever had an allergic reaction to any other pain reliever/fever reducer
2. for at least 7 days after tonsillectomy or oral surgery unless directed by a doctor

Ask a doctor before use if

1. stomach bleeding warning applies to you
2. you have a history of stomach problems, such as heartburn
3. you have high blood pressure, heart disease, liver cirrhosis, or kidney disease
4. you are taking a diuretic
5. you have asthma

Ask a doctor or pharmacist before use if you are

taking a prescription drug for

- gout
- diabetes
- arthritis

Stop use and ask a doctor if

- an allergic reaction occurs. Seek medical help right away.
- you experience any of the following signs of stomach bleeding:
  - feel faint
  - vomit blood
  - have bloody or black stools
  - have stomach pain that does not get better
- pain gets worse or lasts more than 10 days
- fever gets worse or lasts more than 3 days
- redness or swelling is present
- new symptoms occur
- ringing in the ears or a loss of hearing occurs

These could be signs of a serious condition

If pregnant or breast-feeding,

ask a health professional before use. It is especially important not to use aspirin at 20 weeks or later in pregnancy unless definitely directed to do so by a doctor because it may cause problems in the unborn child or complications during delivery.

Keep out of reach of children.

In case of overdose, get medical help or contact a Poison Control Center right away (1-800-222-1222).

Directions

1. drink a full glass of water with each dose
2. adults and children 12 years and over: take 4 to 8 chewable tablets every 4 hours not to exceed 48 tablets in 24 hours unless directed by a doctor
3. children under 12 years: consult a doctor

Other information

1. store at 20-25°C (68-77°F)

Inactive ingredients

corn starch, dextrose excipient, FD&C yellow no. 6 aluminum lake, flavors, saccharin sodium

Principal Display Panel

GOODSENSE®

Chewable

See New Warning

Aspirin Regimen

Talk to your doctor or other healthcare provider before using this product for your heart.

Aspirin 81 mg

Actual Size

Pain Reliever (NSAID)

Orange Flavor

Low Dose

36 Tablets

Compare to active ingredient of Bayer® Chewable Aspirin